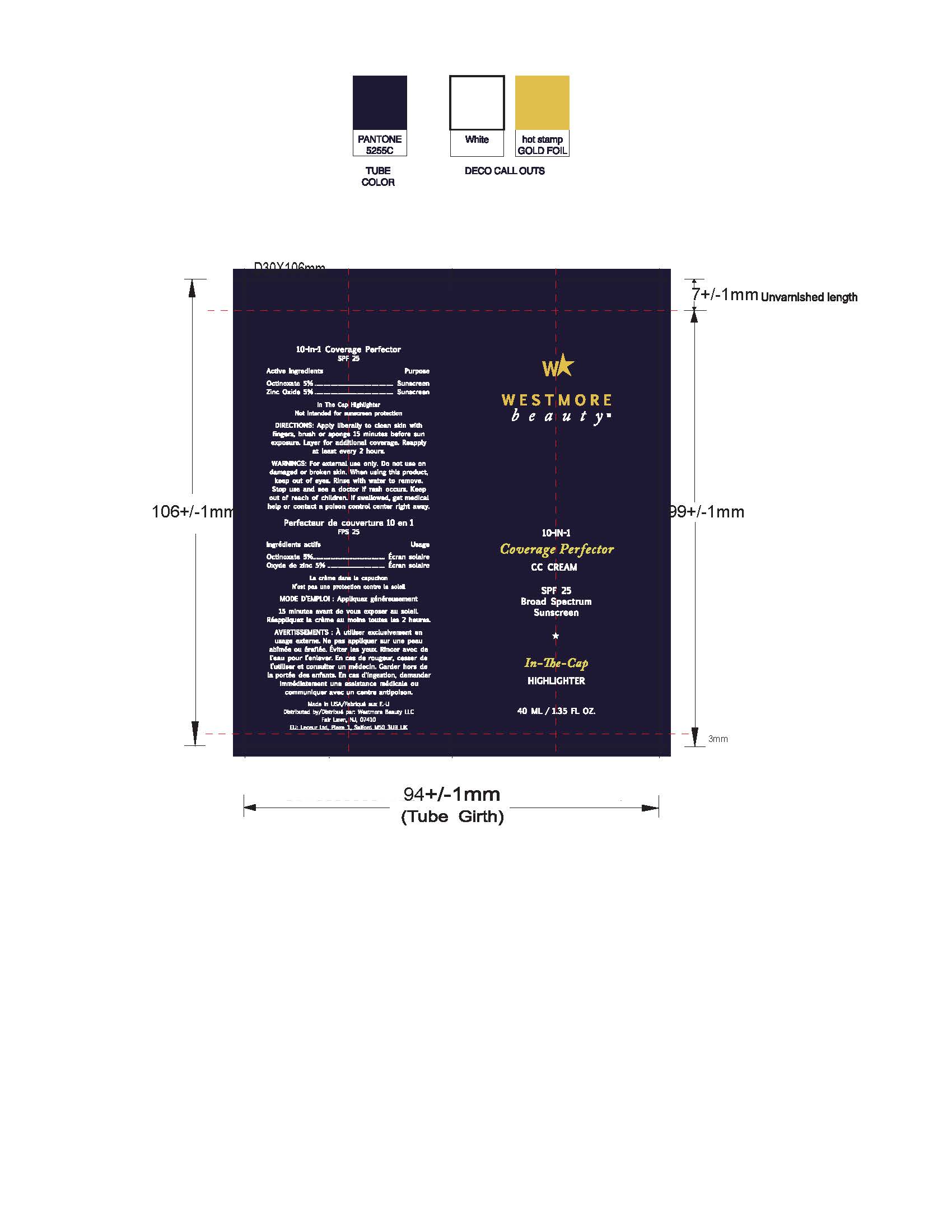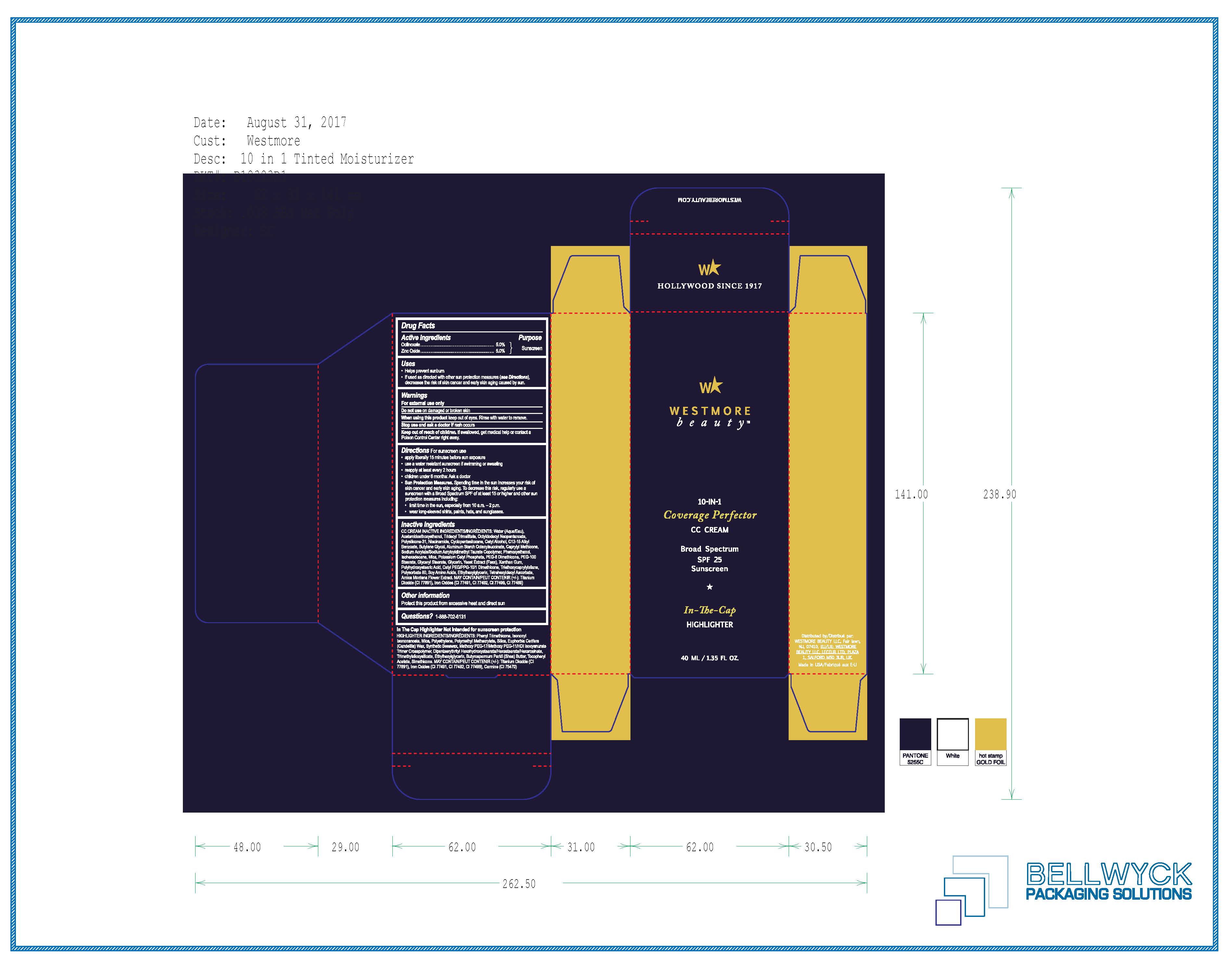 DRUG LABEL: cream
NDC: 61354-070 | Form: CREAM
Manufacturer: Oxygen Development LLC
Category: otc | Type: HUMAN OTC DRUG LABEL
Date: 20230210

ACTIVE INGREDIENTS: ZINC OXIDE 5 mg/100 mg; OCTINOXATE 5 mg/100 mg
INACTIVE INGREDIENTS: ALKYL (C12-15) BENZOATE; NIACINAMIDE; GLYCERIN; GLYCERYL MONOSTEARATE; PEG-8 DIMETHICONE; POTASSIUM CETYL PHOSPHATE; OCTYLDODECYL NEOPENTANOATE; BUTYLENE GLYCOL; CAPRYLYL TRISILOXANE; PHENOXYETHANOL; ACETAMIDOETHOXYETHANOL; ALUMINUM STARCH OCTENYLSUCCINATE; TRIDECYL TRIMELLITATE; SODIUM ACRYLATE/SODIUM ACRYLOYLDIMETHYLTAURATE COPOLYMER (4000000 MW); ISOHEXADECANE; PEG-100 STEARATE; WATER; POLYSILICONE-15; CETYL ALCOHOL; CYCLOMETHICONE 5

Westmore Beauty 10-in-1 coverage perfector CC cream broad spectrum spf 25 sunscreen - Deep

active ingredients

Octinoxate 5%, Zinc Oxide 5%. Purpose: Sunscreen

purpose

sunscreen

uses

- helps prevent sunburn
- If used as directed with other sun protection measure (see directions), decreases the risk of skin cancer and early skin aging caused by sun

warnings

for external use only

do not use

on damage or broken skin

when using this product

keep out of eyes. rinse with water to remove

stop use

and ask a doctor if rash occurs

keep out of reach of children

If swallowed, get medical help or contact a poison control center right away

Directions

- Apply liberally 15 mins before sun exposure
- use a water resistant sunscreen if swimming or sweating
- reapply at least every 2 hours
- children under 6 months: ask a doctor

sun protection measures

spending time in the sun increases your risk of skin cancer and early skin aging. To decrease this risk, regularly use a sunscreen with a broad spectrum SPF of at least 15 or higher and other sun protection measures including:

- limit time in the sun, especially from 10am - 2pm
- wear long-sleeved shirts, pants, hats, and sunglasses

inactive ingredients

water (aqua/eau), Acetamidoethoxyethanol, Tridecyl Trimellitate, Octyldodecyl Neopentanoate, polysilicone-31, niacinimide, Cyclopentasiloxane, Cetyl Alcohol, C12-15 Alkyl Benzoate, Butylene Glycol, Aluminum Starch Octenylsuccinate, Caprylyl Methicone, Sodium Acrylate/Sodium Acryloyldimethyl Taurate Copolymer, Phenoxyethanol, Isohexadecane, mica, Potassium Cetyl Phosphate, Peg-8 Dimethicone, PEG-100 Stearate, Glyceryl Stearate, glycerin, yeast extract, xanthan gum, Polyhydroxystearic Acid, Cetyl PEG/PPG-10/1 Dimethicone, Triethoxycaprylylsilane, polysorbate 80, soy amino acids, Ethylhexylglycerin, Tetrahexyldecyl Ascorbate, Arnica Montana Flower Extract.

other information

protect this product from excessive heat and direct sun